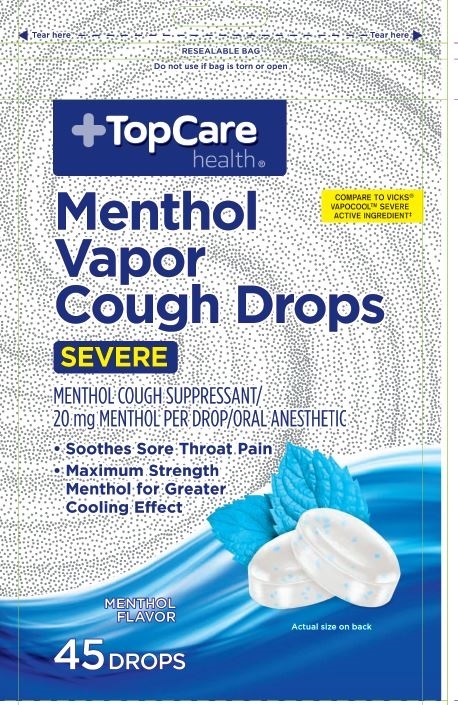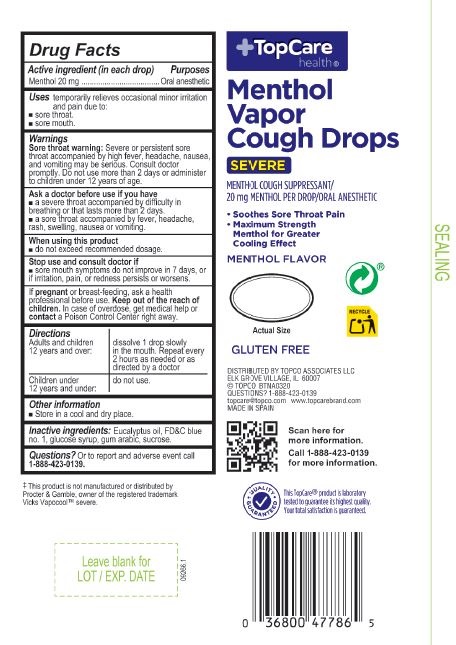 DRUG LABEL: Menthol Vapor Cough Drops
NDC: 72628-108 | Form: PASTILLE
Manufacturer: BOSTON NUTRACEUTICAL PRODUCTION, S.L
Category: otc | Type: HUMAN OTC DRUG LABEL
Date: 20241007

ACTIVE INGREDIENTS: MENTHOL 20 mg/1 1
INACTIVE INGREDIENTS: EUCALYPTUS OIL; SUCROSE; WATER; CORN SYRUP; FD&C BLUE NO. 1; ACACIA

Menthol Vapo Cough Drops
Severe
Menthol Cough Suppressant
20 mg MENTHOL per drop/ Oral Anesthetic

Active Ingredient in each drop Purposes

Menthol 20 mg

Severe

Menthol Caugh Suppressant

Oral Anesthetic

Purposes

Temporarily relieves ocassional minor irritation and pain due to:

- sore throat
- sore mouth

Purposes

Temporarily relieves ocassional minor irritation and pain due to:

- sore throat
- sore mouth

Warnings

Sore throat warning: severe or persistent throat accompanied by high fever headache, nausea and vomiting maybe serious. Consult a doctor promptly. Do not use more than 2 days or administer to children under 12 years of old.

Ask a doctor before use if you have

- A severe throat accompanied by difficulty in breathing or that last more than 2 days
- A severe throat accompanied by fever, headache, rash, swealling, nausea or vomiting.

Stop use and consult doctor if

- sore mouth symptons does not improve in 7 days or if irritation, pain or redness persists or worse

If pregnant or breast feeding, ask a health professional before use.

PREGNANCY OR BREAST FEEDING

If pregnant or breast-feeding, ask a health professional before use.

KEEP OUT OF REACH OF CHILDREN

Keep this and all drugs out of the reach of children.

OVERDOSAGE

In case of accidental overdose, get medical help or contact a Poison Control Center right away.

Directions

- Adults and children 12 years and over: dissolve 1 drop slowly in mouth. Repeated every two hours as needed or as directed by a doctor.
- Children 12 years or under do not use

Other information

- Store in a cool and dry place

INACTIVE INGREDIENT

corn syrup, sucrose, water, eucalyptus oil, acacia, FD&Blue No.1

Questions or comments call: 1-888-423-0139